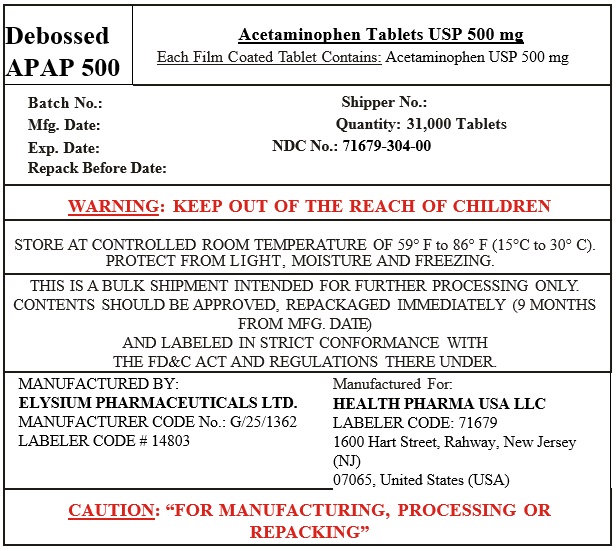 DRUG LABEL: Pain Reliever
NDC: 71679-304 | Form: TABLET, FILM COATED
Manufacturer: Health Pharma USA LLC
Category: otc | Type: HUMAN OTC DRUG LABEL
Date: 20251009

ACTIVE INGREDIENTS: ACETAMINOPHEN 500 mg/1 1
INACTIVE INGREDIENTS: HYPROMELLOSE 2910 (5 MPA.S); HYPROMELLOSE 2910 (15 MPA.S); MAGNESIUM STEARATE; MICROCRYSTALLINE CELLULOSE; POLYETHYLENE GLYCOL, UNSPECIFIED; POVIDONE; STARCH, CORN; STEARIC ACID; TALC; TITANIUM DIOXIDE

Active ingredient (in each tablet)

Acetaminophen 500 mg

Purpose

Pain reliever/Fever reducer

Uses:

- temporarily relieves minor aches and pains due to:
- headache
- muscular aches
- backache
- minor pain from arthritis
- the common cold
- toothache
- temporarily reduces fever
- premenstrual and menstrual cramps

Warnings

Liver warning: This product contains acetaminophen. The maximum daily dose of this product is 6 tablets (3000 mg) in 24 hours. Severe liver damage may occur if you take

- more than 4000 mg of acetaminophen in 24 hours
- with other drugs containing acetaminophen
- 3 or more alcoholic drinks every day while using this product

Allergy alert:Acetaminophen may cause severe skin reactions. Symptoms may include:

- skin reddening
- blisters
- rash

If a skin reaction occurs, stop use and seek medical help right away.

Do not use

- With any other drug containing acetaminophen (prescription or nonprescription). If you are not sure whether a drug contains acetaminophen, ask a doctor or pharmacist.
- If you are allergic to acetaminophen or any of the inactive ingredients in this product.

Ask a doctor before use if you have

liver disease

Ask a doctor or pharmacist before use if you are

taking the blood thinning drug warfarin

Stop use and ask a doctor if:

- pain gets worse or lasts more than 10 days
- fever gets worse or lasts more than 3 days
- new symptoms occur
- redness or swelling is present

These could be signs of a serious condition.

If pregnant or breast-feeding,

ask a health professional before use.

Keep out of reach of children.

Overdose warning: Taking more than recommended dose (overdose) may cause liver damage. In case of overdose, get medical help or contact a Poison Control Center (1-800-222-1222) right away. Quick medical attention is critical for adults as well as for children even if you do not notice any signs or symptoms.

Directions

- do not take more than directed (see overdose warning)
- adults and children 12 years of age and over:
- take 2 caplets every 6 hours while symptoms last
- do not take mote than 6 tablets in 24 hours
- do not use for more than 10 days unless directed by a doctor
- children under 12 years of age: do not use

Other information

- store at 15° to 30°C (59° to 86°F)
- read all product information before using

Inactive ingredients

Pregelatinized Starch, Povidone, Stearic Acid powder, Microcrystalline Cellulose, Magnesium Stearate, Hypromellose, Polyethylene Glycol, Titanium Dioxide, Talc

Questions or comments?

Call +1-844-832-1138 Mon - Fri 9 AM - 5 PM EST